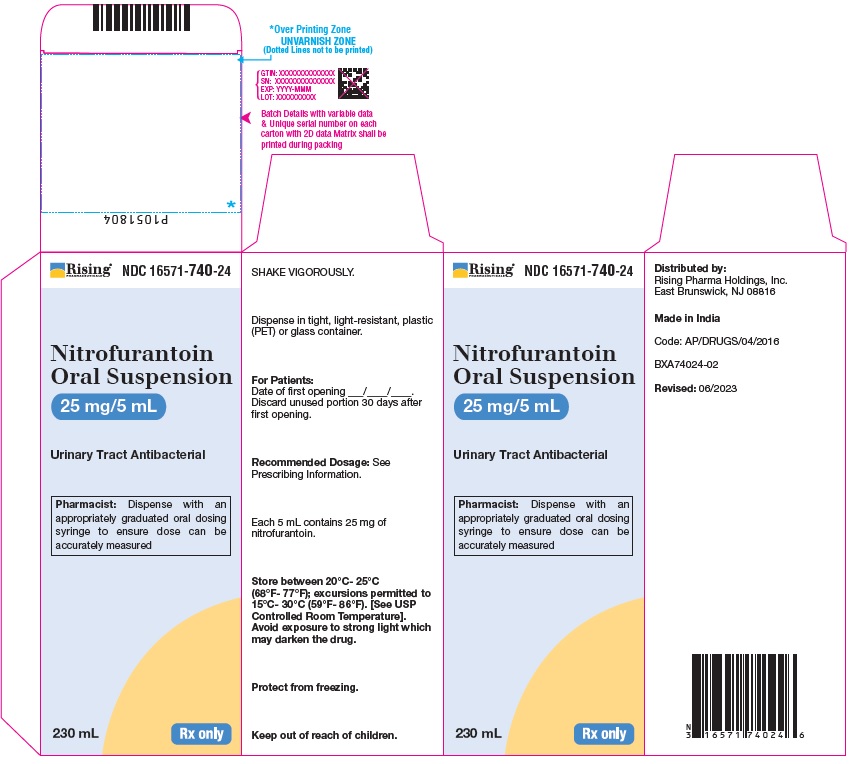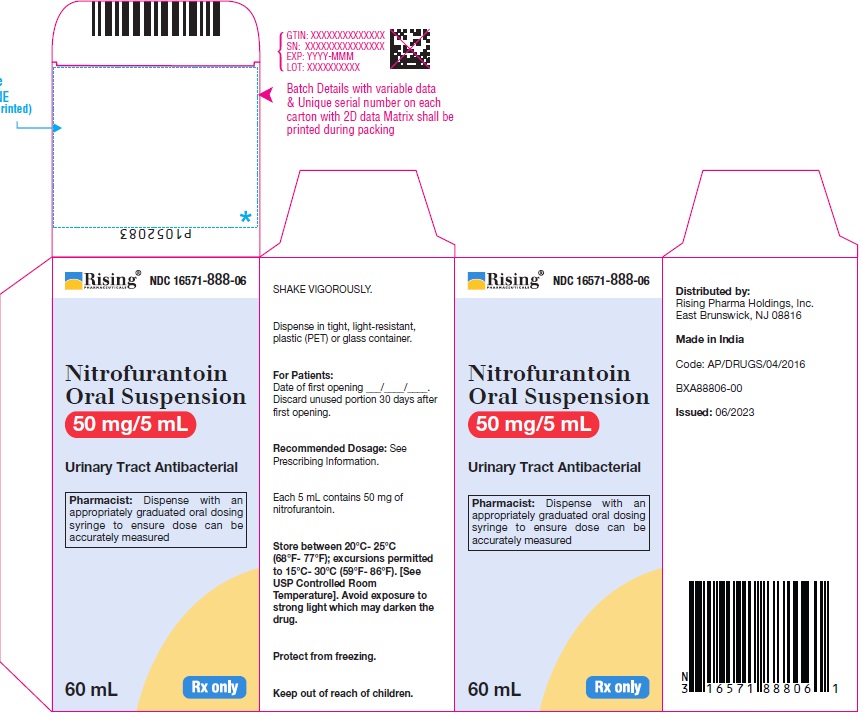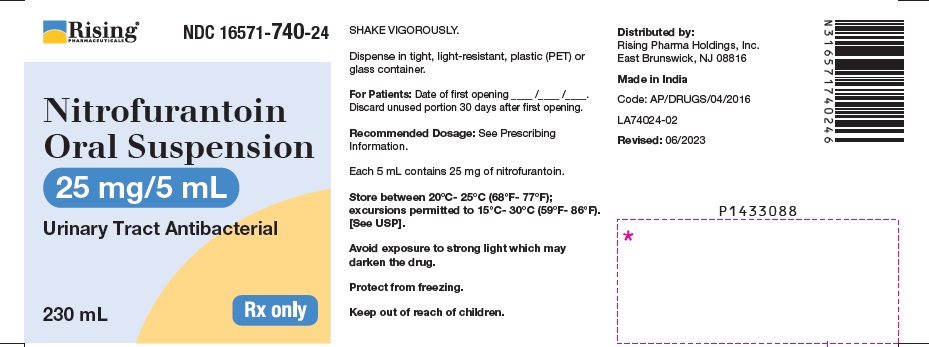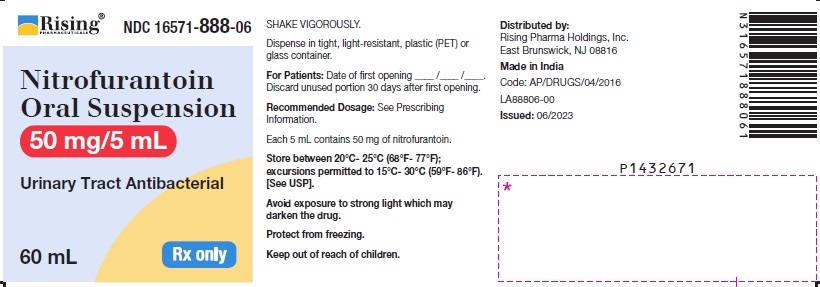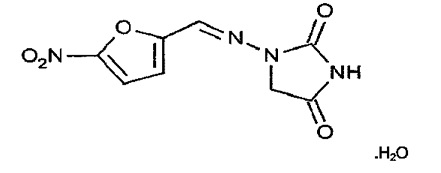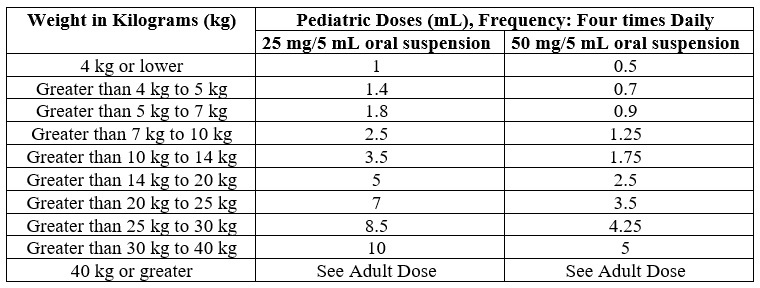 DRUG LABEL: Nitrofurantoin
NDC: 16571-740 | Form: SUSPENSION
Manufacturer: Rising Pharma Holdings, Inc.
Category: prescription | Type: Human Prescription Drug Label
Date: 20251111

ACTIVE INGREDIENTS: NITROFURANTOIN 25 mg/5 mL
INACTIVE INGREDIENTS: CARBOXYMETHYLCELLULOSE SODIUM; CITRIC ACID MONOHYDRATE; GLYCERIN; MAGNESIUM ALUMINUM SILICATE; METHYLPARABEN; PROPYLPARABEN; WATER; SODIUM CITRATE; SORBITOL

HIGHLIGHTS OF PRESCRIBING INFORMATION

These highlights do not include all the information needed to use NITROFURANTOIN ORAL SUSPENSION safely and effectively. See full prescribing information for NITROFURANTOIN ORAL SUSPENSION.
NITROFURANTOIN oral suspension
Initial U.S. Approval: 1953

RECENT MAJOR CHANGES

Dosage and Administration (2) 1/2024

1 INDICATIONS & USAGE

Nitrofurantoin is a nitrofuran antibacterial indicated in adults and pediatric patients 1 month of age and older for the treatment of urinary tract infections caused by susceptible bacteria. (1)
Limitations of Use
Nitrofurantoin is not indicated for the treatment of pyelonephritis or perinephric abscesses. (1)
Usage
To reduce the development of drug-resistant bacteria and maintain the effectiveness of nitrofurantoin oral suspension and other antibacterial drugs, nitrofurantoin oral suspension should be used only to treat or prevent infections that are proven or strongly suspected to be caused by susceptible bacteria. (1)

2 DOSAGE & ADMINISTRATION

- Adult Patients: 50 mg to 100 mg four times a day - the lower dosage level is recommended for uncomplicated urinary tract infections. (2.2)
- Pediatric Patients: 5 mg/kg to 7 mg/kg of body weight per 24 hours, given in four divided doses (contraindicated under one month of age). (2.3)

3 DOSAGE FORMS & STRENGTHS

Oral Suspension: 25 mg/5 mL and 50 mg/5 mL. (3)

4 CONTRAINDICATIONS

• Known hypersensitivity to nitrofurantoin. (4)
• History of cholestatic jaundice/hepatic dysfunction associated with nitrofurantoin. (4)
• Patients who have anuria, oliguria, or significant impairment of renal function (creatinine clearance under 60 mL per minute or clinically significant elevated serum creatinine). (4)
• Pregnant patients at term (38 weeks to 42 weeks gestation), during labor and delivery, or when the onset of labor is imminent. (4)
• Pediatric Patients under one month of age. (4)

5 WARNINGS AND PRECAUTIONS

• Hypersensitivity Reactions: Serious and occasionally fatal hypersensitivity (anaphylactic) reactions have been reported in patients receiving nitrofurantoin oral suspension. If signs and symptoms of a hypersensitivity reaction occurs, immediately discontinue nitrofurantoin oral suspension. (5.1)

• Pulmonary Reactions: Discontinue if sign and symptoms of pulmonary reactions occur and take appropriate measures. (5.2)

• Hepatotoxicity: Discontinue if signs/symptoms of hepatitis occur. Monitor liver function tests. (5.3)

• Neuropathy: Peripheral neuropathy has occurred. (5.4)

• Hemolytic Anemia: Discontinue if sign and symptoms of hemolysis occur. (5.5)

• Clostridioides difficile-associated diarrhea: Evaluate patients if diarrhea occurs. (5.6)

6 ADVERSE REACTIONS

The most common adverse reactions occurring in patients are nausea, vomiting, anorexia, vertigo, nystagmus, dizziness, headache, angioedema, rash, urticaria, pulmonary hypersensitivity reactions, hepatic reactions, peripheral neuropathy, increased aspartate aminotransferase, increased alanine aminotransferase, decreased hemoglobin, increased serum phosphorus, and eosinophilia (6)
To report SUSPECTED ADVERSE REACTIONS, contact Rising Pharma Holdings, Inc. at 1-844–874–7464 or FDA at 1-800-FDA-1088 or www.fda.gov/medwatch.

7 DRUG INTERACTIONS

- Antacids: Decreased absorption of nitrofurantoin. (7.1)
- Uricosuric drugs: Inhibit renal tubular secretion of nitrofurantoin. (7.2)

8 USE IN SPECIFIC POPULATIONS

• Lactation: Breastfeeding is not recommended in infants under one month of age or with glucose-6-phosphate dehydrogenase (G6PD) deficiency. (8.2)
• Pediatric Use: Nitrofurantoin oral suspension is contraindicated in pediatric patients under one month of age. (8.4)

FULL PRESCRIBING INFORMATION

1 INDICATIONS & USAGE

Nitrofurantoin oral suspension is indicated in adults and pediatric patients 1 month of age and older for the treatment of urinary tract infections due to susceptible strains of Escherichia coli, Enterococcus species, Staphylococcus aureus, Klebsiella species and Enterobacter species.
Limitations of Use
Nitrofurantoin oral suspension is not indicated for the treatment of pyelonephritis or perinephric abscesses [see Warnings and Precautions (5.7)].
Usage
To reduce the development of drug-resistant bacteria and maintain the effectiveness of nitrofurantoin oral suspension and other antibacterial drugs, nitrofurantoin oral suspension should be used only to treat or prevent infections that are proven or strongly suspected to be caused by susceptible bacteria. When culture and susceptibility information are available, they should be considered in selecting or modifying antibacterial therapy. In the absence of such data, local epidemiology and susceptibility patterns may contribute to the empiric selection of therapy.

2 DOSAGE & ADMINISTRATION

2.1 Recommended Dosage and Administration in Adult Patients

The recommended dosage is 50 mg to 100 mg of nitrofurantoin oral suspension four times a day.
For long-term suppressive therapy in adults, a reduction of dosage to 50 mg to 100 mg at bedtime may be adequate. The benefits of long-term suppressive therapy should be balanced against the increased potential for systemic toxicity and for the development of antibacterial resistance [see Warnings and Precautions (5.2, 5.4, 5.6)].
Administer nitrofurantoin oral suspension with food to improve drug absorption [see Clinical Pharmacology (12.3)] and, in some patients, tolerance.

2.2 Recommended Dosage and Administration in Pediatric Patients (1 month of age and older)

The recommended dosage of nitrofurantoin oral suspension is 5 mg/kg to 7 mg/kg of body weight per 24 hours, given in four divided doses in pediatric patients aged 1 month and older. Administer nitrofurantoin oral suspension with food to improve drug absorption [see Clinical Pharmacology (12.3)] and, in some patients, tolerance.
Table 1 lists individual dosage volumes for two different strengths of nitrofurantoin oral suspension (25 mg/5 mL and 50 mg/5 mL) based on body weight for pediatric patients.
Table 1: Nitrofurantoin Oral Suspension Pediatric Dosing Table for Pediatric Patients 1 month of Age and Older

To measure the correct pediatric doses, it is important to administer nitrofurantoin oral suspension with an appropriate size oral dosing syringe with graduations that align with the volume prescribed in Table 1 above.
Continue therapy for one week or for at least 3 days after sterility of the urine is obtained. Continued infection indicates the need for reevaluation.
For long-term suppressive therapy in pediatric patients, doses as low as 1 mg/kg per 24 hours, given in a single dose or in two divided doses, may be adequate [see Warnings and Precautions (5.2, 5.4, 5.6)].

3 DOSAGE FORMS & STRENGTHS

Nitrofurantoin oral suspension is available as an opaque, yellow liquid oral suspension containing 25 mg/5 mL and 50 mg/5 mL of nitrofurantoin.

4 CONTRAINDICATIONS

Nitrofurantoin oral suspension is contraindicated in:
• patients with known hypersensitivity to nitrofurantoin [see Warnings and Precautions (5.1)].
• patients with a previous history of cholestatic jaundice/hepatic dysfunction associated with nitrofurantoin [see Warnings and Precautions (5.3)].
• patients who have anuria, oliguria, or significant impairment of renal function (creatinine clearance under 60 mL per minute or clinically significant elevated serum creatinine) due to an increased risk of toxicity resulting from impaired excretion of the drug [see Warnings and Precautions (5.4)].
• pregnant patients at term (38 weeks to 42 weeks gestation), during labor and delivery, or when the onset of labor is imminent and in pediatric patients younger than 1 month of age because of the possibility of hemolytic anemia due to immature erythrocyte enzyme systems (glutathione instability) [see Warnings and Precautions (5.5) and Use in Specific Populations (8.1 and 8.4)].

5 WARNINGS AND PRECAUTIONS

5.1 Hypersensitivity Reactions

Serious and occasionally fatal hypersensitivity (anaphylactic) reactions have been reported in patients receiving nitrofurantoin oral suspension [see Adverse Reactions (6)]. If signs and symptoms of a hypersensitivity reaction occurs, immediately discontinue nitrofurantoin oral suspension and initiate appropriate medications and/or supportive care. Nitrofurantoin oral suspension is contraindicated in patients with known hypersensitivity to nitrofurantoin.

5.2 Pulmonary Reactions

Acute, subacute, or chronic pulmonary reactions have been reported in patients treated with nitrofurantoin. If these reactions occur, discontinue nitrofurantoin and take appropriate measures. Reports have cited pulmonary reactions as a contributing cause of death.
Chronic pulmonary reactions (diffuse interstitial pneumonitis or pulmonary fibrosis, or both) can develop insidiously. These reactions occur generally in patients receiving therapy for six months or longer. Close monitoring of the pulmonary condition of patients receiving long-term therapy is warranted and requires that the benefits of therapy be weighed against potential risks [see Adverse Reactions (6)].

5.3 Hepatotoxicity

Hepatic reactions, including hepatitis, cholestatic jaundice, chronic active hepatitis, and hepatic necrosis, has occurred. Fatalities have been reported. The onset of chronic active hepatitis may be insidious. Monitor patients periodically for changes in biochemical tests that would indicate liver injury. If hepatitis occurs, discontinue nitrofurantoin oral suspension immediately, and take appropriate measures.

5.4 Neuropathy

Peripheral neuropathy, which may become severe or irreversible, has occurred. Fatalities have been reported. Conditions such as renal impairment (creatinine clearance under 60 mL per minute or clinically significant elevated serum creatinine), anemia, diabetes mellitus, electrolyte imbalance, vitamin B deficiency, and debilitating disease may enhance the occurrence of peripheral neuropathy. Monitor patients receiving long-term therapy periodically for changes in renal function.
Optic neuritis has been reported with nitrofurantoin formulations [see Adverse Reactions (6)].

5.5 Hemolytic Anemia

Cases of hemolytic anemia of the primaquine-sensitivity type have been induced by nitrofurantoin. Hemolysis appears to be linked to a glucose-6-phosphate dehydrogenase deficiency in the red blood cells of the affected patients. This deficiency is found in 10 percent of Blacks and a small percentage of ethnic groups of Mediterranean and Near-Eastern origin. If hemolysis occurs, discontinue nitrofurantoin oral suspension immediately; hemolysis ceases when the drug is withdrawn.

5.6 Clostridioides difficile-associated Diarrhea

Clostridioides difficile-associated Diarrhea (CDAD) has been reported with use of nearly all antibacterial agents, including nitrofurantoin oral suspension, and may range in severity from mild diarrhea to fatal colitis. Treatment with antibacterial agents alters the normal flora of the colon leading to overgrowth of C. difficile.
C. difficile produces toxins A and B which contribute to the development of CDAD. Hypertoxin producing strains of C. difficile cause increased morbidity and mortality, as these infections can be refractory to antibacterial therapy and may require colectomy. CDAD must be considered in all patients who present with diarrhea following antibacterial use. Careful medical history is necessary since CDAD has been reported to occur over two months after the administration of antibacterial agents.
If CDAD is suspected or confirmed, ongoing antibacterial use not directed against C. difficile may need to be discontinued. Appropriate fluid and electrolyte management, protein supplementation, antibacterial treatment of C. difficile, and institute surgical evaluation as clinically indicated.

5.7 Persistence or Reappearance of Bacteriuria

Nitrofurantoin lacks the broader tissue distribution of other therapeutic agents approved for urinary tract infections. Consequently, many patients who are treated with nitrofurantoin are predisposed to persistence or reappearance of bacteriuria. If persistence or reappearance of bacteriuria occurs with symptoms of urinary tract infection, after treatment with nitrofurantoin, other therapeutic agents with broader tissue distribution should be selected. In considering the use of nitrofurantoin, lower eradication rates should be balanced against the increased potential for systemic toxicity and for the development of antibacterial resistance when agents with broader tissue distribution are utilized.

6 ADVERSE REACTIONS

The following clinically significant adverse reactions are discussed in more detail in other sections of the labeling:
• Hypersensitivity Reactions [see Warnings and Precautions (5.1)]
• Pulmonary Reactions [see Warnings and Precautions (5.2)]
• Hepatotoxicity [see Warnings and Precautions (5.3)]
• Neuropathy [see Warnings and Precautions (5.4)]
• Hemolytic anemia [see Warnings and Precautions (5.5)]
• Clostridioides difficile-associated Diarrhea [see Warnings and Precautions (5.6)]
• Persistence or Reappearance of Bacteriuria [see Warnings and Precautions (5.7)]
The following adverse reactions associated with the use of nitrofurantoin formulations, including, nitrofurantoin oral suspension were identified in clinical studies or post-marketing reports. Because some of these reactions were reported voluntarily from a population of uncertain size, it is not always possible to reliably estimate their frequency or establish a causal relationship to drug exposure.
Respiratory: chronic, subacute, or acute pulmonary hypersensitivity reactions have occurred.
Chronic pulmonary reactions have occurred generally in patients who have received continuous treatment for six months or longer. Malaise, dyspnea on exertion, cough, and altered pulmonary function are common manifestations which can occur insidiously. Radiologic and histologic findings of diffuse interstitial pneumonitis or fibrosis, or both, are also common manifestations of the chronic pulmonary reaction. Fever is prominent.
The severity of chronic pulmonary reactions and their degrees of resolution appear to be related to the duration of therapy after the first clinical signs appear. Pulmonary function may be impaired permanently, even after cessation of therapy. The risk is greater when chronic pulmonary reactions are not recognized early.
In subacute pulmonary reactions, fever and eosinophilia occur less often than in the acute form. Upon cessation of therapy, recovery may require several months. If the symptoms are not recognized as being drug-related and nitrofurantoin therapy is not stopped, the symptoms may become more severe.
Acute pulmonary reactions are commonly manifested by fever, chills, cough, chest pain, dyspnea, pulmonary infiltration with consolidation of pleural effusion on x-ray, and eosinophilia. Acute reactions usually occur within the first week of treatment and are reversible with cessation of therapy. Resolution often is dramatic.
Changes in EKG (e.g., non-specific ST/T wave changes, bundle branch block) have been reported in association with pulmonary reactions.
Cyanosis has been reported.
Hepatic: Hepatic reactions, including hepatitis, cholestatic jaundice, chronic active hepatitis, and hepatic necrosis, have occurred.
Neurologic: Peripheral neuropathy, which may become severe or irreversible, has occurred. Fatalities have been reported. Conditions such as renal impairment (creatinine clearance under 60 mL per minute or clinically significant elevated serum creatinine), anemia, diabetes mellitus, electrolyte imbalance, vitamin B deficiency, and debilitating diseases may increase the possibility of peripheral neuropathy.
Asthenia, vertigo, nystagmus, dizziness, headache, and drowsiness also have been reported with the use of nitrofurantoin.
Benign intracranial hypertension (pseudotumor cerebri), confusion, depression, optic neuritis, and psychotic reactions have been reported. Bulging fontanels, as a sign of benign intracranial hypertension in infants, have been reported rarely.
Dermatologic: Exfoliative dermatitis and erythema multiforme (including Stevens-Johnson syndrome) have been reported. Alopecia also has been reported.
Allergic: A lupus-like syndrome associated with pulmonary reactions to nitrofurantoin has been reported. Also, angioedema; maculopapular, erythematous, or eczematous eruptions; pruritus; urticaria; anaphylaxis; arthralgia; myalgia; drug fever; and vasculitis (sometimes associated with pulmonary reactions) have been reported. Hypersensitivity reactions present the most frequent spontaneously-reported adverse reactions in worldwide post marketing experience with nitrofurantoin formulations, including nitrofurantoin oral suspension.
Gastrointestinal: Nausea, emesis, and anorexia occur most often. Abdominal pain and diarrhea are less common gastrointestinal reactions. These dose-related reactions can be minimized by reduction of dosage. Sialadenitis and pancreatitis have been reported. There have been sporadic reports of pseudomembranous colitis with the use of nitrofurantoin. The onset of pseudomembranous colitis symptoms may occur during or after antibacterial treatment.
Hematologic: Cyanosis secondary to methemoglobinemia has been reported.
Miscellaneous: As with other antibacterial agents, superinfections caused by resistant organisms, e.g., Pseudomonas species or Candida species, can occur. There are sporadic reports of Clostridioides difficile superinfections, or pseudomembranous colitis, with the use of nitrofurantoin, including nitrofurantoin oral suspension.
Laboratory Adverse Reactions
The following laboratory adverse reactions have been reported with the use of nitrofurantoin formulations, including nitrofurantoin oral suspension; increased AST (SGOT), increased ALT (SGPT), decreased hemoglobin, increased serum phosphorus, eosinophilia, glucose-6-phosphate dehydrogenase deficiency anemia, agranulocytosis, leukopenia, granulocytopenia, hemolytic anemia, thrombocytopenia, megaloblastic anemia. In most cases, these hematologic abnormalities resolved following cessation of therapy. Aplastic anemia has been reported.

7 DRUG INTERACTIONS

7.1 Antacids

Antacids containing magnesium trisilicate, when administered concomitantly with nitrofurantoin, reduce both the rate and extent of absorption. The mechanism for this interaction probably is adsorption of nitrofurantoin onto the surface of magnesium trisilicate. If coadministration of nitrofurantoin with antacids containing magnesium trisilicate cannot be avoided, monitor for lack of efficacy [see Clinical Pharmacology (12.3)].

7.2 Uricosuric Drugs

Uricosuric drugs, such as probenecid and sulfinpyrazone, can inhibit renal tubular secretion of nitrofurantoin. The resulting increase in nitrofurantoin serum levels may increase toxicity, and the decreased urinary levels could lessen its efficacy as a urinary tract antibacterial. Therefore, monitor for nitrofurantoin adverse reactions when co-administering nitrofurantoin oral suspension with uricosuric drugs.

7.3 Drug Interference with Laboratory Tests

The presence of nitrofurantoin can cause a false-positive reaction for glucose in the urine when using Benedict's or Fehling's copper reduction reaction to determine the amount of reducing substances like glucose in the urine. Use glucose tests based on enzymatic glucose oxidase reactions to detect glucose in the urine.

8 USE IN SPECIFIC POPULATIONS

8.1 Pregnancy

Risk Summary
Nitrofurantoin is contraindicated in pregnant women at term (38 weeks to 42 weeks gestation), during labor and delivery, or when the onset of labor is imminent because of the possibility of hemolytic anemia in the infant (see Clinical Considerations).
Published epidemiological studies, including cohort studies and case control studies, have reported inconsistent findings related to nitrofurantoin use during the first trimester and risk of major birth defects. These studies cannot definitively establish the presence or absence of risk due to several methodological limitations. The limited number of epidemiological studies available have not identified drug-associated risks of major birth defects, miscarriage or other adverse maternal or fetal outcomes.
In animal reproduction studies, no fetotoxicity was observed when nitrofurantoin was administered orally to pregnant rats and rabbits, during organogenesis, at up to 6 times the recommended human dose (see Data).
The background risk of major birth defects and miscarriage for the indicated population is unknown. All pregnancies have a background risk of birth defect, loss, or other adverse outcomes. In the U.S. general population, the estimated background risk of major birth defects and miscarriage in clinically recognized pregnancies is 2% to 4% and 15% to 20%, respectively.
Clinical Considerations
Fetal/Neonatal Adverse Reactions
Nitrofurantoin is not recommended in pregnant women at term (38 weeks to 42 weeks gestation), during labor and delivery, or when the onset of labor is imminent because of the possibility of hemolytic anemia due to immature erythrocyte enzyme systems (glutathione instability) [see Contraindications (4) and Warnings and Precautions (5.4)].
Data
Animal Data
Several reproduction studies have been performed in rabbits and rats at doses up to six times the human dose and have revealed no harm to the fetus due to nitrofurantoin. In a single published study conducted in mice at 68 times the human dose (based on mg/kg administered to the dam), growth retardation and a low incidence of minor and common malformations were observed. However, at 25 times the human dose, fetal malformations were not observed.
Nitrofurantoin has been shown in one published transplacental carcinogenicity study to induce lung papillary adenomas in the F1 generation mice at doses 19 times the human dose on a mg/kg basis. The relationship of this finding to potential human carcinogenesis is presently unknown.

8.2 Lactation

Risk Summary
Nitrofurantoin is present in human breast milk following oral administration. There are insufficient data on the effect of nitrofurantoin on milk production.
Infants less than one month of age or who have glucose-6-phosphate dehydrogenase (G6PD) deficiency are at risk for hemolytic anemia from nitrofurantoin exposure. Therefore, breastfeeding is not recommended in these infants.
In a breastfed infant over the age of one month and with normal G6PD, the developmental and health benefits of breastfeeding should be considered along with the mother’s clinical need for nitrofurantoin and any potential adverse effects on the breastfed infant from nitrofurantoin or from the underlying maternal condition. Monitor these infants for vomiting, diarrhea, and rash.

8.3 Females and Males of Reproductive Potential

Infertility
Male
Based on findings from a fertility study conducted in 36 healthy male volunteers and an animal fertility study, nitrofurantoin may reversibly decrease spermatogenesis [see Nonclinical Toxicology (13.1)]. Nitrofurantoin doses of 10 mg/kg/day or greater in healthy human males may produce a slight to moderate spermatogenic arrest with a decrease in sperm count. The effect on fertility is unknown.

8.4 Pediatric Use

Nitrofurantoin oral suspension is contraindicated in pediatric patients younger than 1 month of age because of the possibility of hemolytic anemia due to immature erythrocyte enzyme systems (glutathione instability). [see Contraindications (4) and Warnings and Precautions (5.4)].
The safety and effectiveness of nitrofurantoin in pediatric patients aged 1 month of age and older for the treatment of urinary tract infections have been established.

10 OVERDOSAGE

Incidents of acute overdosage of nitrofurantoin have resulted in symptoms such as vomiting. Induction of emesis is recommended. There is no specific antidote, but a high fluid intake should be maintained to promote urinary excretion of the drug. Nitrofurantoin is dialyzable.

11 DESCRIPTION

Nitrofurantoin oral suspension contains nitrofurantoin, a synthetic nitrofuran antibacterial agent specific for urinary tract infections. The chemical name is 1-[[(5-nitro-2-furanyl)methylene]amino]-2,4-imidazolidinedione monohydrate. The molecular formula is C8H6N4O5ꞏH2O and the molecular weight is 256.17. The structural formula is:

Nitrofurantoin is a stable, yellow, crystalline compound.
Nitrofurantoin oral suspension is available as an opaque, yellow liquid suspension for oral administration containing 25 mg/5 mL and 50 mg/5 mL of nitrofurantoin. Nitrofurantoin oral suspension also contains the following inactive ingredients: carboxymethylcellulose sodium, citric acid, flavors, glycerin, magnesium aluminum silicate, methylparaben, propylparaben, purified water, sodium citrate, and sorbitol.

12 CLINICAL PHARMACOLOGY

12.1 Mechanism of Action

Nitrofurantoin is an antibacterial drug [see Microbiology (12.4)].

12.2 Pharmacodynamics

Pharmacodynamic effects of nitrofurantoin are unknown.

12.3 Pharmacokinetics

Absorption
Orally administered nitrofurantoin is readily absorbed. Blood concentrations at therapeutic dosage are usually low.
Effect of Food
The presence of food or agents delaying gastric emptying can increase the bioavailability of nitrofurantoin.
Distribution
Nitrofurantoin is highly soluble in urine. Nitrofurantoin lacks the broader tissue distribution of other therapeutic agents approved for urinary tract infections.
Elimination
Excretion
Nitrofurantoin is rapidly excreted in urine, to which it may impart a brown color.
Following a dose regimen of 100 mg four times a day for 7 days, average urinary drug recoveries (0 hour to 24 hours) on Day 1 and Day 7 were 42.7% and 43.6%.
Nitrofurantoin is dialyzable.
Specific Populations
The pharmacokinetics of nitrofurantoin oral suspension are unknown for the geriatric patients, pediatric patients, patients with hepatic impairment, or pregnant women. Differences between male and female patients, and racial or ethnic groups are unknown.
Patients with Renal Impairment
The reported urinary recoveries of nitrofurantoin after a single 100 mg oral dose and 100 mg four times a day in patients with varying renal function showed approximate linear relationship between the amount of nitrofurantoin recovered and creatinine clearance.
Drug Interaction Studies
Antacids such as magnesium trisilicate
In a cross-over study, the in vivo absorption characteristics of nitrofurantoin and nitrofurantoin-magnesium trisilicate combination were evaluated in 6 healthy males. The administration of 5 g magnesium trisilicate with 100 mg nitrofurantoin reduced the rate and extent of nitrofurantoin excretion reflecting decrease in both rate and extent of its absorption [see Drug Interaction (7.1)].
Propantheline
In a crossover study, the in vivo absorption characteristics of nitrofurantoin and propantheline (an anticholinergic agent) combination were evaluated in six subjects. Administration of 30 mg of propantheline 45 min prior to nitrofurantoin 100 mg administration resulted in a statistically significant increase in nitrofurantoin excretion, however, the clinical significance of this effect is unknown.

12.4 Microbiology

Mechanism of Action
Nitrofurantoin is reduced by a wide range of enzymes including bacterial flavoproteins to reactive intermediates which are damaging to macromolecules such as DNA and proteins.
Resistance
Nitrofurantoin is not active against most strains of Proteus species or Serratia species. It has no activity against Pseudomonas species. Although cross-resistance with other antibacterials may occur, cross resistance with sulfonamides has not been observed.
Interaction with Other Antibacterials
Antagonism has been demonstrated in vitro between nitrofurantoin and quinolones.
Antibacterial Activity
Nitrofurantoin has been shown to be active against most of the following bacteria both in vitro and in clinical infections:
Aerobic bacteria
Gram-positive bacteria
Staphylococcus aureus
Enterococcus species
Gram-negative bacteria
Escherichia coli
Enterobacter species
Klebsiella species
The following in vitro data are available, but their clinical significance is unknown. Nitrofurantoin exhibits in vitro activity against the following bacteria; however, the safety and efficacy of nitrofurantoin in treating clinical infections due to these bacteria have not been established in adequate and well-controlled clinical trials.
Aerobic bacteria
Gram-positive bacteria
Coagulase-negative staphylococci (including Staphylococcus epidermidis and Staphylococcus saprophyticus)
Streptococcus agalactiae
Viridans group streptococci
Gram-negative bacteria
Citrobacter koseri
Citrobacter freundii
Klebsiella oxytoca
Susceptibility Testing
For specific information regarding susceptibility test interpretive criteria, and associated test methods and quality control standards recognized by FDA for this drug, please see: http://www.fda.gov/STIC.

13 NONCLINICAL TOXICOLOGY

13.1 Carcinogenesis & Mutagenesis & Impairment Of Fertility

Carcinogenesis
Nitrofurantoin was not carcinogenic when fed to female Holtzman rats for 44.5 weeks or to female Sprague-Dawley rats for 75 weeks. Two chronic rodent bioassays utilizing male and female Sprague-Dawley rats and two chronic bioassays in Swiss mice and in BDF1 mice revealed no evidence of carcinogenicity.
Nitrofurantoin presented evidence of carcinogenic activity in female B6C3F1 mice as shown by increased incidences of tubular adenomas, benign mixed tumors, and granulosa cell tumors of the ovary. In male F344/N rats, there were increased incidences of uncommon kidney tubular cell neoplasms, osteosarcomas of the bone, and neoplasms of the subcutaneous tissue.
The significance of carcinogenicity findings relative to the therapeutic use of nitrofurantoin in humans is unknown.
Mutagenesis
Nitrofurantoin has been shown to induce point mutations in certain strains of Salmonella typhimurium and forward mutations in L5178Y mouse lymphoma cells. Nitrofurantoin induced increased numbers of sister chromatid exchanges and chromosomal aberrations in Chinese hamster ovary cells but not in human cells in culture. Results of the sex-linked recessive lethal assay in Drosophila were negative after administration of nitrofurantoin by feeding or by injection. Nitrofurantoin did not induce heritable mutation in the rodent models examined.
The significance of mutagenicity findings relative to the therapeutic use of nitrofurantoin in humans is unknown.
Impairment of Fertility
The administration of high doses of nitrofurantoin to rats causes temporary spermatogenic arrest; this is reversible on discontinuing the drug.

16 HOW SUPPLIED/STORAGE AND HANDLING

How Supplied
Nitrofurantoin oral suspension (25 mg/5 mL) is available in:
NDC 16571-740-24 PET amber bottle of 230 mL
Nitrofurantoin oral suspension (50 mg/5 mL) is available in:
NDC 16571-888-06 PET amber bottle of 60 mL
Storage and Handling
Avoid exposure to strong light which may darken the drug. It is stable when stored between 20°C to 25°C (68°F to 77°F); excursions permitted to 15°C to 30°C (59°F to 86°F) [See USP Controlled Room Temperature]. Protect from freezing. Shake vigorously. Dispense in tight, light-resistant, plastic (PET) or glass container.
Use within 30 days.

17 PATIENT COUNSELING INFORMATION

Administration Instructions
Instruct the patients to:
• complete the full course of therapy; however, advise the patients or their caregiver to contact their physician if any unusual symptoms occur during therapy.
• take daily doses of nitrofurantoin oral suspension with food, as food will further enhance tolerance and improve the absorption of the drug.
• shake nitrofurantoin oral suspension vigorously before use each time.
• use an oral dosing syringe to correctly measure the prescribed amount of nitrofurantoin oral suspension. Inform patients or caregivers that an appropriate size oral dosing syringe with graduations that align with the volume prescribed may be obtained from their pharmacy.
Serious Allergic Reactions
Advise patients that allergic reactions, including serious allergic reactions, could occur with nitrofurantoin oral suspension and that serious reactions require immediate treatment. Advise patients to discontinue nitrofurantoin oral suspension at the first sign of allergic reactions [see Warnings and Precautions (5.1)].
Diarrhea
Advise patients that diarrhea is a common problem caused by antibacterial drugs, including nitrofurantoin oral suspension which usually ends when the antibacterial drug is discontinued. Sometimes frequent watery and bloody diarrhea (with or without stomach cramps and fever) may occur even as late as two or more months after having taken the last dose of the antibacterial drug. If this occurs, advise patients to contact their physician as soon as possible [see Warnings and Precautions (5.6)].
Drug Interactions with Antacids
Advise patients not to use antacid preparations containing magnesium trisilicate while taking nitrofurantoin oral suspension [see Drug Interactions (7.1)].
Lactation
Advise women not to breastfeed infants who are less than one month of age or who have G6PD deficiency during treatment with nitrofurantoin oral suspension [see Use in Specific Populations (8.2)].
Antibacterial Resistance
Patients should be counseled that antibacterial drugs including nitrofurantoin should only be used to treat bacterial infections. They do not treat viral infections (e.g., the common cold). When nitrofurantoin oral suspension is prescribed to treat a bacterial infection, patients should be told that although it is common to feel better early in the course of the therapy, the medication should be taken exactly as directed. Skipping doses or not completing the full course of therapy may (1) decrease the effectiveness of the immediate treatment and (2) increase the likelihood that bacteria will develop resistance and will not be treatable by nitrofurantoin or other antibacterial drugs in the future.
Change in Urine Color
Inform patients that nitrofurantoin oral suspension may impart a brown color to their urine [see Clinical Pharmacology (12.3)].

Distributed by:
Rising Pharma Holdings, Inc.
East Brunswick, NJ 08816
Made in India
Code: AP/DRUGS/04/2016
Revised: 02/2024
PIA88806-01

PACKAGE LABEL.PRINCIPAL DISPLAY PANEL

Rising ® NDC 16571-740-24
Nitrofurantoin Oral Suspension
25 mg/5 mL
Urinary Tract Antibacterial
230 mL Rx only
Carton label

Container Label

Rising ® NDC 16571-888-06
Nitrofurantoin Oral Suspension
50 mg/5 mL
Urinary Tract Antibacterial
60 mLRx only
Carton label

Container label